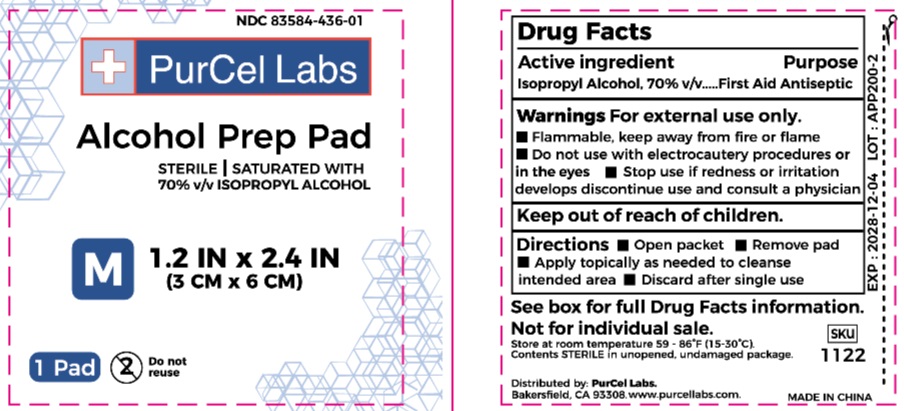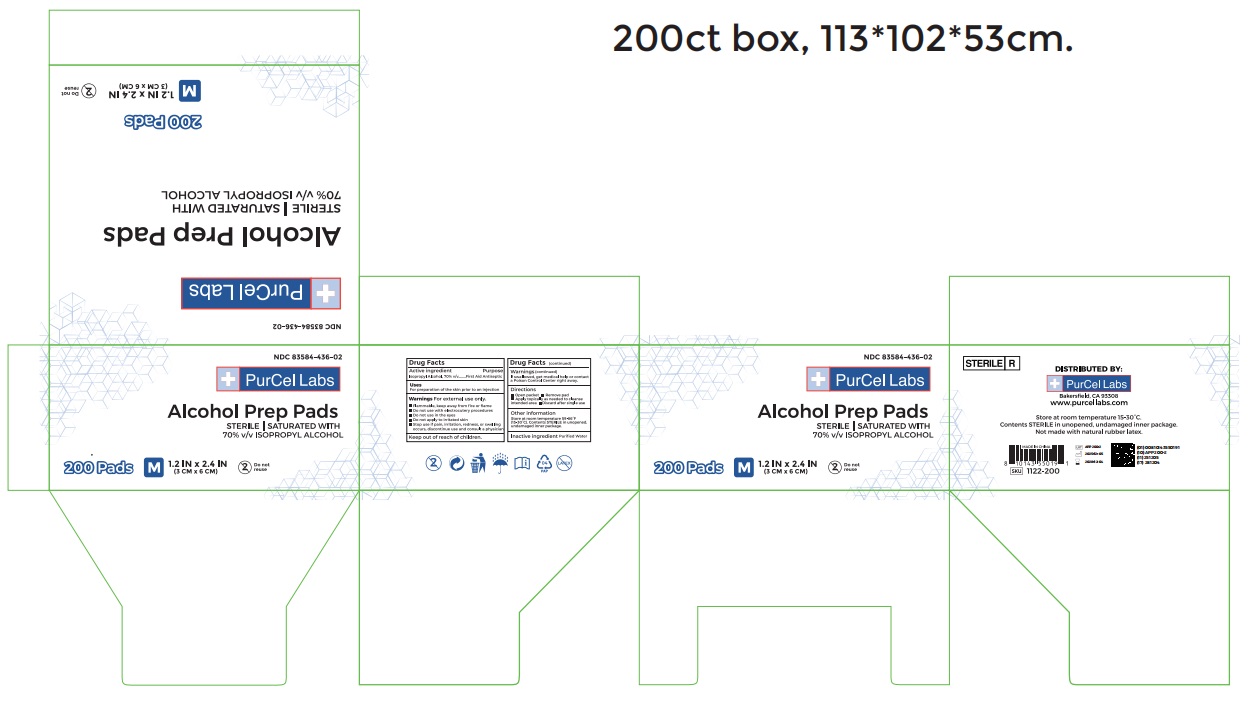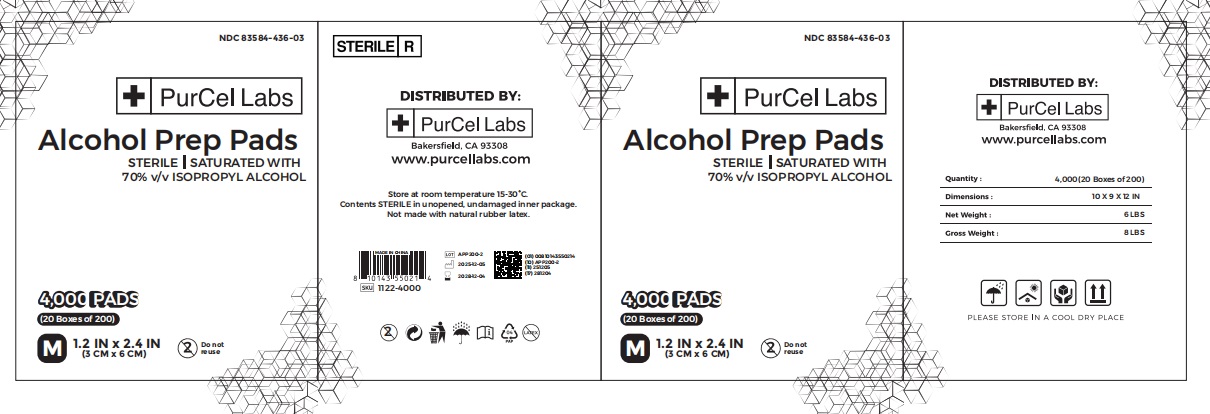 DRUG LABEL: ALCOHOL PREP PAD
NDC: 83584-436 | Form: SWAB
Manufacturer: PurCel Labs LLC
Category: otc | Type: HUMAN OTC DRUG LABEL
Date: 20251203

ACTIVE INGREDIENTS: ISOPROPYL ALCOHOL 70 mL/100 mL
INACTIVE INGREDIENTS: WATER

83584-436

Active ingredient

lsopropyl Alcohol, 70% v/v

Purpose

First Aid Antiseptic

Warnings

For external use only.

Flammable,keep away from fire or flame

Do not use with electrocautery procedures or in the eyes

Stop use if redness or irritation develops discontinue use and consult a physician

Keep out of reach of children

Directions

Open packet

Remove pad

Appl topically as needed to cleanse intended area

Discard after single use

Use

Used for skin disinfection

Inactive Ingredients

water

OTHER SAFETY INFORMATION

Store at room tomperature 59 -86'F(15-30'C)